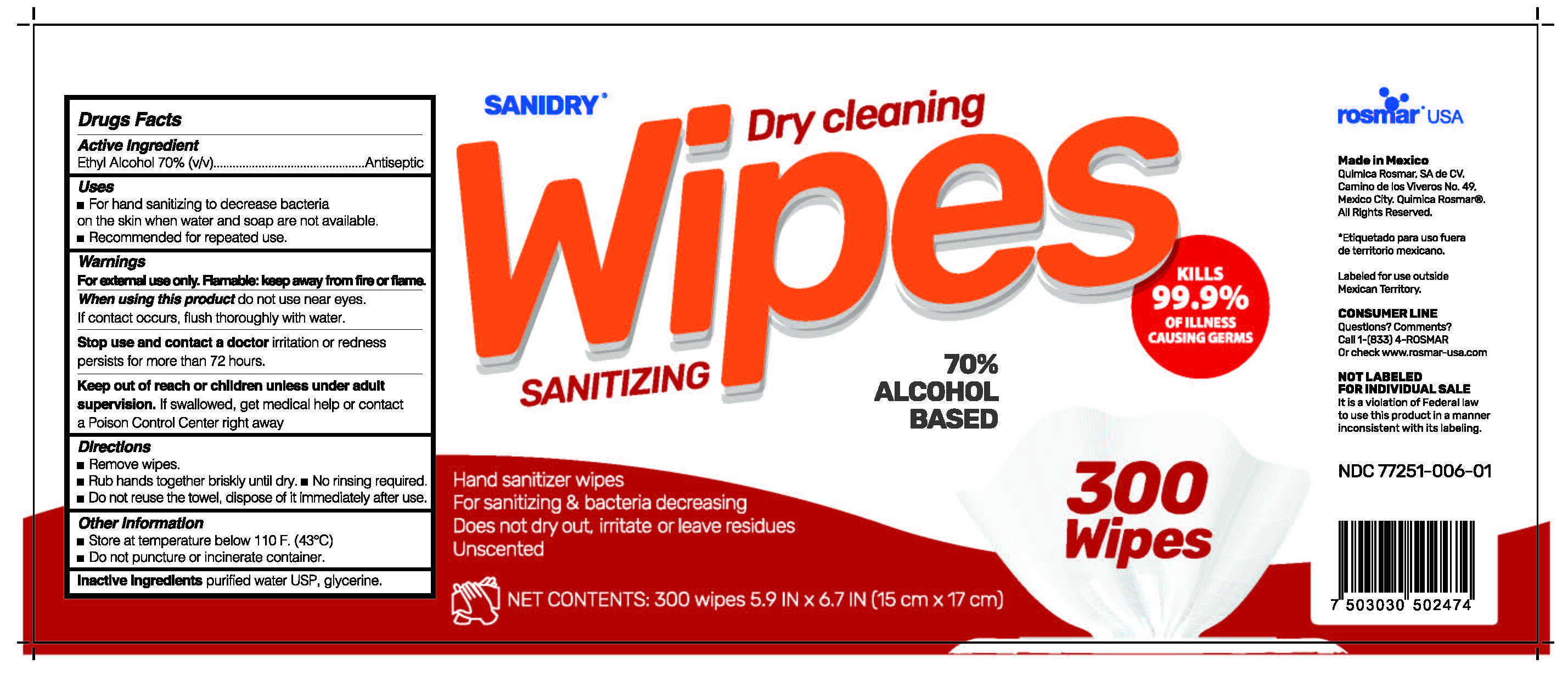 DRUG LABEL: Sanidry
NDC: 77251-006 | Form: CLOTH
Manufacturer: QUIMICA ROSMAR S.A. DE C.V.
Category: otc | Type: HUMAN OTC DRUG LABEL
Date: 20210118

ACTIVE INGREDIENTS: ALCOHOL 70 mL/100 mL
INACTIVE INGREDIENTS: GLYCERIN; WATER

77251-006 Sanidry
Alcohol 70%

This is a hand sanitizer manufactured according to the Temporary Policy for Preparation of Certain Alcohol-Based Hand Sanitizer Products During the Public Health Emergency (CoViD-19); Guidance for Industry.

The hand sanitizer is manufactured using only the following United States Pharmacopoeia (USP) grade ingredients in the preparation of the product (percentage in final product formulation) consistent with World Health Organization (WHO) recommendations:

1. Alcohol (ethanol) (USP or Food Chemical Codex (FCC) grade) (80%, volume/volume (v/v)) in an aqueous solution denatured according to Alcohol and Tobacco Tax and Trade Bureau regulations in 27 CFR part 20.
2. Glycerol (1.45% v/v).
3. Hydrogen peroxide (0.125% v/v).
4. Sterile distilled water or boiled cold water.

The firm does not add other active or inactive ingredients. Different or additional ingredients may impact the quality and potency of the product.

Active Ingredient(s)

Alcohol 70% v/v. Purpose: Antiseptic

Purpose

Antiseptic, Hand Sanitizer

Use

For hand sanitizing to decrease bacteria on the skin when water and soap are not available.

Recommended for repeated use.

Warnings

For external use only. Flammable. Keep away from fire or flame

- Do not use near eyes.

When using this product, do not use near eyes. If contact occurs, flush thoroughly with water.

Stop use and contact a doctor if irritation or redness persists for more than 72 hours

Keep out of reach of children unless under adult supervision. If swallowed, get medical help or contact a Poison Control Center right away.

Directions

- Remove wipes
- Rub hands together briskly until dry. No rinsing required.
- Do not reuse the towel, dispose of it immediately after use.

Other information

- Store at temperature below 110F(43C)
- Do not puncture or incinerate container

Inactive ingredients

purified water USP, glycerin

RECENT MAJOR CHANGES

Indications and Usage

Dosage and Administration

Active ingredients

Inactive ingredients

Package Label - Principal Display Panel

300 units NDC: 77251-006-01